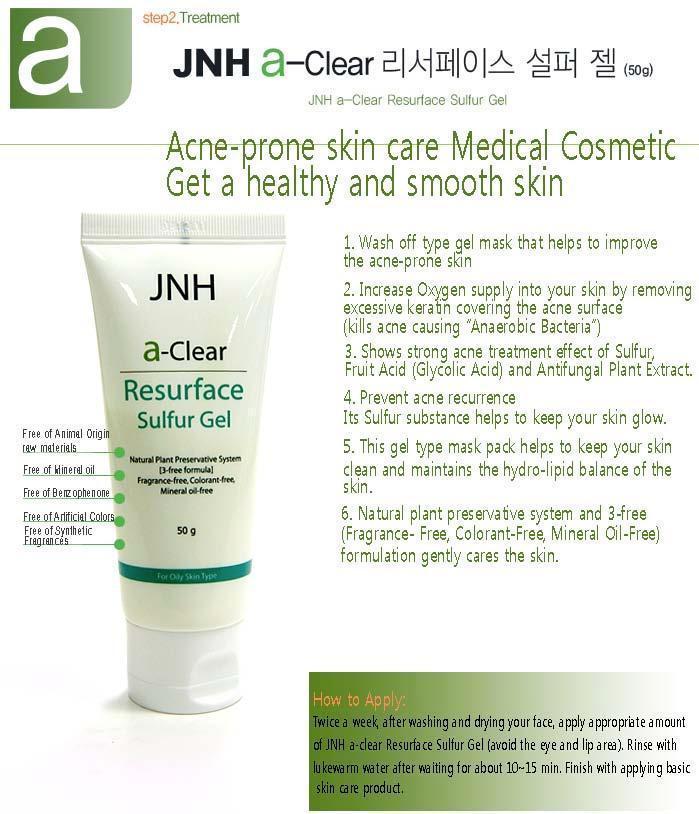 DRUG LABEL: JNH a-Clear Resurface Sulfur
NDC: 53010-4001 | Form: GEL
Manufacturer: Daeduck Lab Co., Ltd.
Category: otc | Type: HUMAN OTC DRUG LABEL
Date: 20141015

ACTIVE INGREDIENTS: GLYCERIN 2 g/100 g
INACTIVE INGREDIENTS: GLYCOLIC ACID; CYCLOMETHICONE 5

Drug Facts

ACTIVE INGREDIENT

glycerin

INACTIVE INGREDIENT

sulfur, glycolic acid, cyclopentasiloxane, portulaca oleracea ext, dimethicone, ppg-15 stearyl ether

PURPOSE

to treat acne

keep out or reach of the children

INDICATIONS AND USAGE

apply appropriate amount twice a week

WARNINGS

1) avoid direct sun exposure, keep it refrigerated or in cooler places
2) gently tap on the packaging a few times before intake

DOSAGE AND ADMINISTRATION

for exernal use only